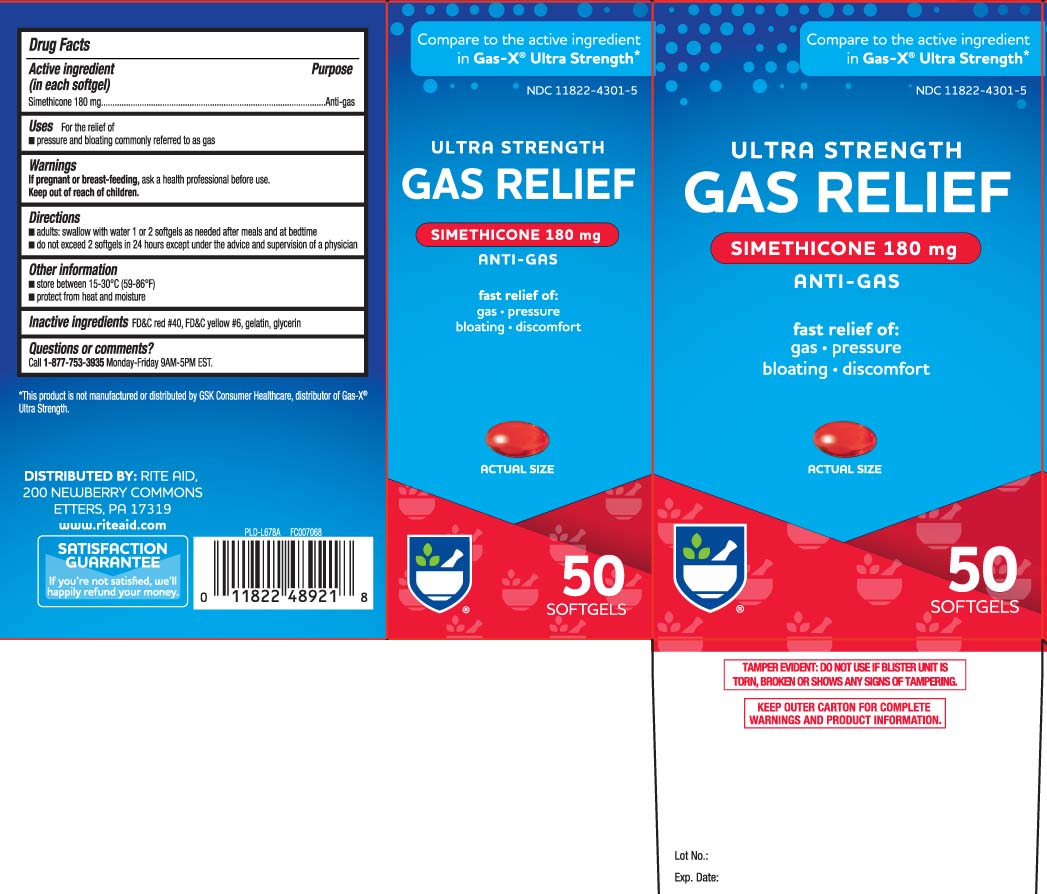 DRUG LABEL: Gas Relief
NDC: 11822-4301 | Form: CAPSULE, LIQUID FILLED
Manufacturer: Rite Aid Corporation
Category: otc | Type: HUMAN OTC DRUG LABEL
Date: 20240508

ACTIVE INGREDIENTS: DIMETHICONE 180 mg/1 1
INACTIVE INGREDIENTS: FD&C RED NO. 40; FD&C YELLOW NO. 6; GELATIN; GLYCERIN

Drug Facts

Active ingredient (in each softgel)

Simethicone 180 mg

Purpose

Antigas

Uses

For the relief of

- pressure and bloating commonly referred to as gas

Warnings

If pregnant or breast-feeding,

ask a health professional before use.

Directions

- adults: swallow with water 1 or 2 softgels as needed after meals and at bedtime
- do not exceed 2 softgels in 24 hours except under the advice and supervision of a physician

Other information

- store between 15-30°C (59-86°F)
- protect from heat and moisture

Inactive ingredients

FD&C red #40*, FD&C yellow #6, gelatin, glycerin

Questions or comments?

Call 1-877-753-3935 Monday-Friday 9AM-5PM EST

Principal Display Panel

Compare to the active ingredient in Gas-X® Ultra Strength*

ULTRA STRENGTH

GAS RELIEF

SIMETHICONE 180 mg

ANTI-GAS

Fast Relief of:

- gas
- pressure
- bloating
- discomfort

SOFTGELS

†This product is not manufactured or distributed by GSK Consumer Healthcare, distributor of Gas-X® Ultra Strength.

TAMPER EVIDENT: DO NOT USE IF BLISTER UNIT IS TORN, BROKEN OR SHOWS ANY SIGNS OF TAMPERING.

KEEP OUTER CARTON FOR COMPLETE WARNINGS AND PRODUCT INFORMATION.

DISTRIBUTED BY: RITE AID,

200 NEWBERRY COMMONS

ETTERS, PA 17319

www.riteaid.com

Package Label

RITE AID Ultra Strength Gas Relief